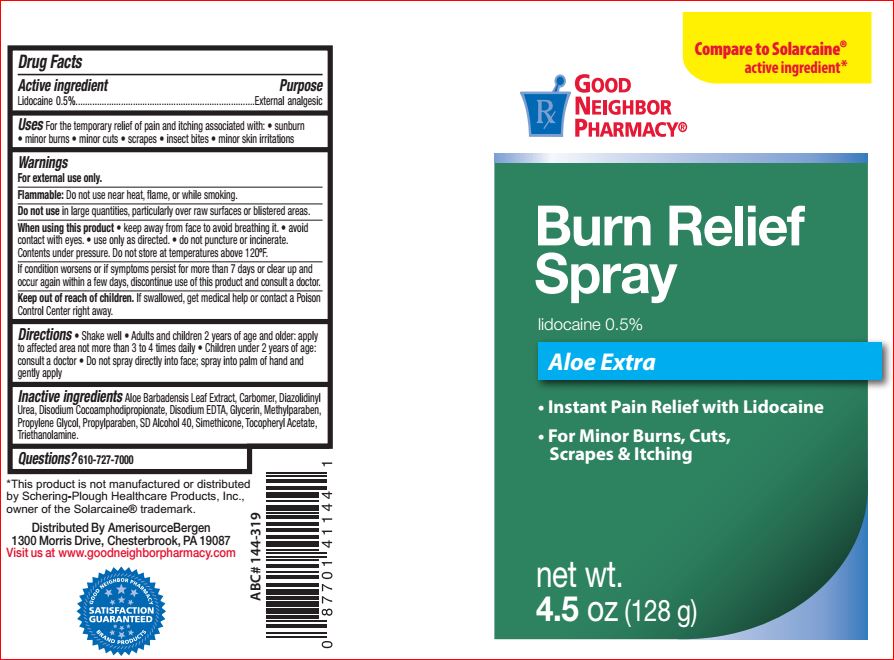 DRUG LABEL: Burn Relief
NDC: 24385-777 | Form: SPRAY
Manufacturer: Amerisource Bergen
Category: otc | Type: HUMAN OTC DRUG LABEL
Date: 20180723

ACTIVE INGREDIENTS: Lidocaine 0.5 g/100 g
INACTIVE INGREDIENTS: Aloe; CARBOMER HOMOPOLYMER TYPE C (ALLYL PENTAERYTHRITOL CROSSLINKED); DIAZOLIDINYL UREA; Disodium Cocoamphodipropionate; EDETATE DISODIUM; Glycerin; Methylparaben; Propylene Glycol; Propylparaben; ALCOHOL; .ALPHA.-TOCOPHEROL ACETATE; TROLAMINE

Drug Facts

Active ingredient Purpose
Lidocaine 0.5%.........................External analgesic

Uses

For the temporary relief of pain and itching associated with: • sunburn
• minor burns • minor cuts • scrapes • insect bites • minor skin irritations

Warnings
For external use only.
Flammable: Do not use near heat, flame, or while smoking.
Do not use in large quantities, particularly over raw surfaces or blistered areas.
When using this product • keep away from face to avoid breathing it. • avoid
contact with eyes. • use only as directed. • do not puncture or incinerate.
Contents under pressure. Do not store at temperatures above 120ºF.
If condition worsens or if symptoms persist for more than 7 days or clear up and
occur again within a few days, discontinue use of this product and consult a doctor.

Keep out of reach of children. If swallowed, get medical help or contact a Poison Control Center right away.

DOSAGE AND ADMINISTRATION

Directions • Shake well • Adults and children 2 years of age and older: apply
to affected area not more than 3 to 4 times daily • Children under 2 years of age:
consult a doctor • Do not spray directly into face; spray into palm of hand and
gently apply

Inactive ingredients

Aloe Barbadensis Leaf Extract, Carbomer, Diazolidinyl
Urea, Disodium Cocoamphodipropionate, Disodium EDTA, Glycerin, Methylparaben,
Propylene Glycol, Propylparaben, SD Alcohol 40, Simethicone, Tocopheryl Acetate,
Triethanolamine.